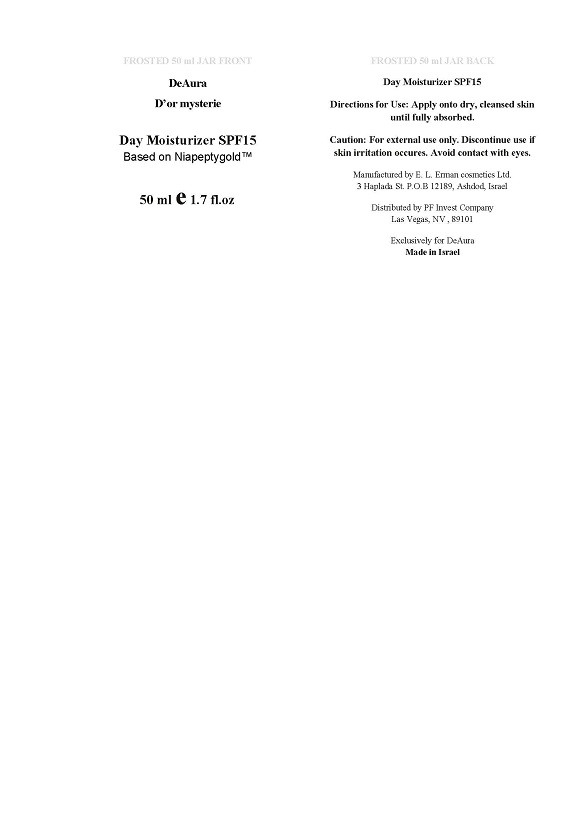 DRUG LABEL: Day Moisturizer SPF 15
NDC: 43638-002 | Form: CREAM
Manufacturer: E.L. Erman Cosmetic Manufacturing Ltd.
Category: otc | Type: HUMAN OTC DRUG LABEL
Date: 20160314

ACTIVE INGREDIENTS: OCTOCRYLENE 2.5 mg/100 mg; AVOBENZONE 1.5 mg/100 mg
INACTIVE INGREDIENTS: PHENOXYETHANOL; STEARIC ACID; ALLANTOIN; CAMELLIA SINENSIS SEED; MACADAMIA OIL; HYDROLYZED WHEAT PROTEIN (ENZYMATIC, 3000 MW); DIMETHICONE 100; JOJOBA ACID; CETEARYL PHOSPHATE; WATER; WHITE WAX; PALMITOYL FRAGMENT; VITIS VINIFERA LEAF OIL; OLEA EUROPAEA (OLIVE) OIL UNSAPONIFIABLES; ALOE VERA FLOWER; MACROCYSTIS PYRIFERA; GLYCERIN; LEPIDIUM SATIVUM SEED; TOCOPHEROL; CALENDULA OFFICINALIS FLOWER; BETULA PAPYRIFERA WHOLE; OENOTHERA BIENNIS; BORAGO OFFICINALIS SEED; SHEA BUTTER; GLUCONOLACTONE; SODIUM BENZOATE; CHAMOMILE; TRIETHYLENE GLYCOL; ROSA CANINA FRUIT OIL; HYALURONIC ACID

ACTIVE INGREDIENTS

Octocrylene 5%

Avobenzone (Butyl Methoxydibenzoyl Methane) 3%

PURPOSE

Sunscreen

INDICATIONS AND USAGE

Moisturizer cream provides deep hydration with UV protection for a beautiful, youth-inspired complexion

KEEP OUT OF REACH OF CHILDREN

If product is swallowed get medical help or contact a Poison Control Center right away

DOSAGE AND ADMINISTRATION

Directions
Apply an even amount of cream onto dry, cleansed skin.
Gently massage in with your fingertips until fully absorbed.

WARNINGS

Skin Cancer/Skin Aging Alert: Spending time in the sun increases your risk of skin cancer and early skin aging. This product has been shown only to prevent sunburn not skin cancer or early skin aging
For external use only
Do not use on damaged or broken skin
When using this product keер out of eyes. Rinse with water to remove.
Stop use and ask a doctor if rash occurs.

INACTIVE INGREDIENTS

Olea Europaea (Olive) Fruit Oil, Cetearyl Alcohol, Cetyl Alcohol, Glycerin, Vitis Vinifera (Grape) Seed Oil,
Cera Alba (Beeswax), Aloe Barbadensis Leaf Juice, Phenoxyethanol, Maris Aqua (Dead Sea Water), Borago Officinalis (Borage)
Seed Oil, Gluconolactone, Water Glycerin Macrocystis Pyrifera Extract Hydrolyzed Wheat Protein PVP, Dimethicone,
Sodium Benzoate, Butyrospermum Parkii (Shea Butter), Calendula Officinalis Flower Oil, Anthemis Nobilis (Chamomile)
Flower Extract, Fragrance (Parfum) , Stearic Acid, Simmondsia Chinensis (Jojoba) Seed Oil, Triethylene Glycol, Allantoin,
Oenothera Biennis (Evening Primrose) Oil, Rosa Canina Fruit Oil, Algae Extract, Camellia Sinensis Leaf Extract,
Macadamia Ternifolia Oil, Tocopheryl Acetate (Vit. E), Hyaluronic Acid, NIAPEPTYGOLD (NIACINAMIDE (VITAMIN B3) WATER
PALMITOYL HEXAPEPTIDE-9 PHENOXYETHANOL UBIQUINONE LEPIDIUM SATIVUM SPROUT EXTRACT CI 77480 (GOLD 24K)).